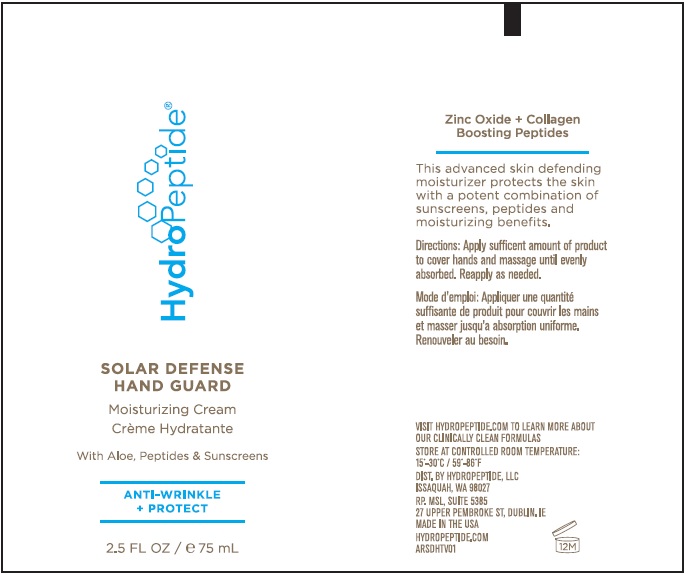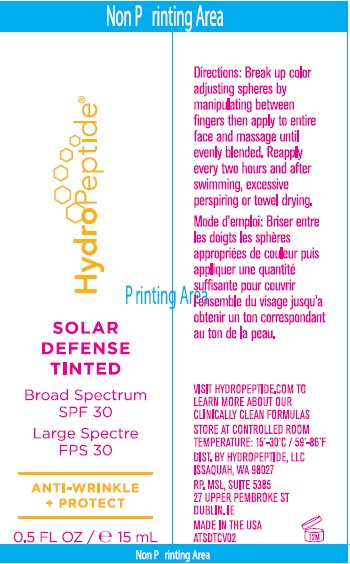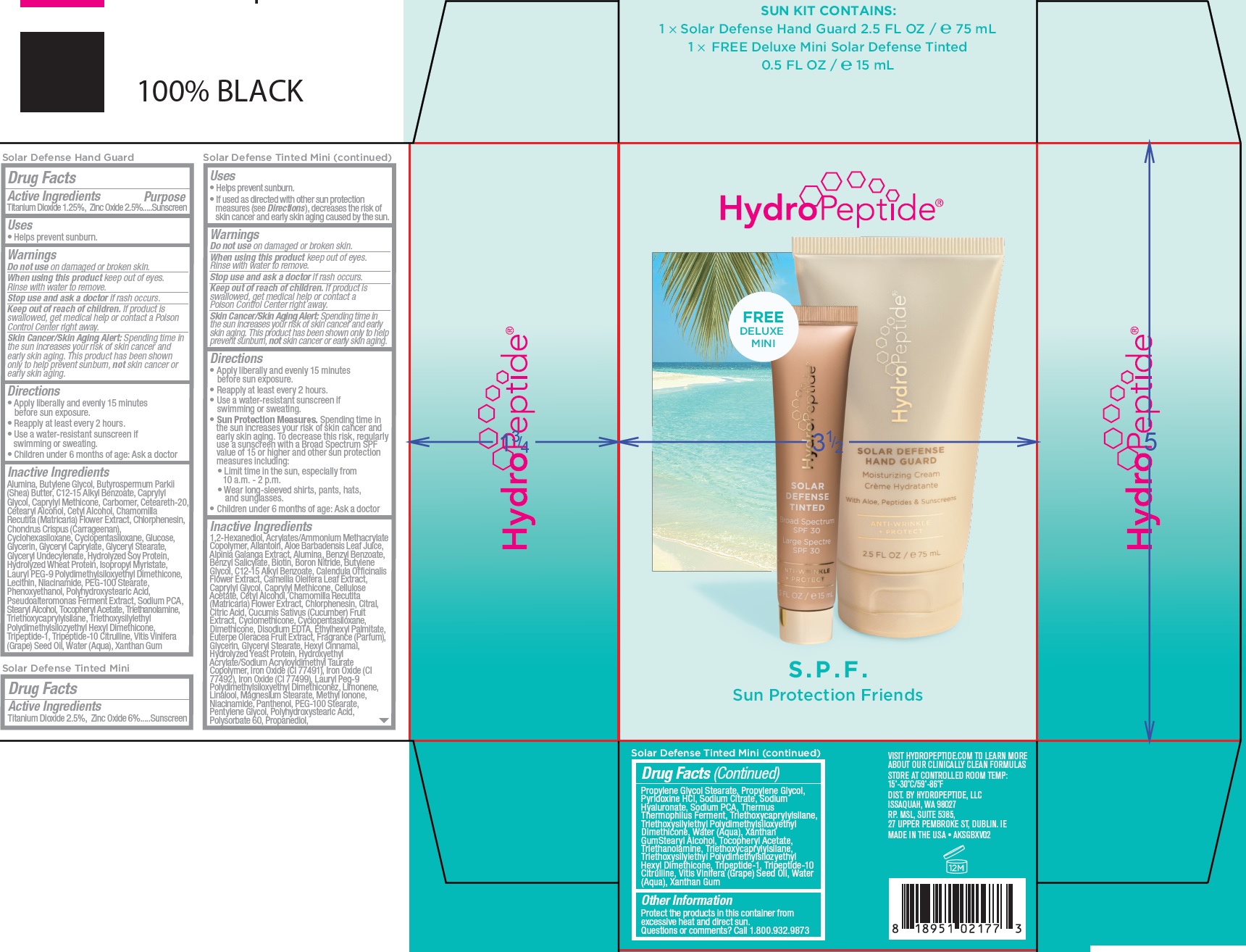 DRUG LABEL: HydroPeptide S.P.F. Sun Protection Friends
NDC: 60934-010 | Form: KIT | Route: TOPICAL
Manufacturer: HydroPeptide LLC
Category: otc | Type: HUMAN OTC DRUG LABEL
Date: 20250128

ACTIVE INGREDIENTS: TITANIUM DIOXIDE 12.5 mg/1 mL; ZINC OXIDE 25 mg/1 mL; TITANIUM DIOXIDE 25 mg/1 mL; ZINC OXIDE 60 mg/1 mL
INACTIVE INGREDIENTS: ALUMINUM OXIDE; BUTYLENE GLYCOL; SHEA BUTTER; ALKYL (C12-15) BENZOATE; CAPRYLYL GLYCOL; CAPRYLYL TRISILOXANE; CARBOMER HOMOPOLYMER, UNSPECIFIED TYPE; POLYOXYL 20 CETOSTEARYL ETHER; CETOSTEARYL ALCOHOL; CETYL ALCOHOL; CHAMOMILE; CHLORPHENESIN; CHONDRUS CRISPUS CARRAGEENAN; CYCLOMETHICONE 6; CYCLOMETHICONE 5; ANHYDROUS DEXTROSE; GLYCERIN; GLYCERYL CAPRYLATE; GLYCERYL MONOSTEARATE; GLYCERYL 1-UNDECYLENATE; HYDROLYZED SOY PROTEIN (ENZYMATIC; 2000 MW); HYDROLYZED WHEAT PROTEIN (ENZYMATIC; 3000 MW); ISOPROPYL MYRISTATE; LAURYL PEG-9 POLYDIMETHYLSILOXYETHYL DIMETHICONE; NIACINAMIDE; PEG-100 STEARATE; PHENOXYETHANOL; SODIUM PYRROLIDONE CARBOXYLATE; STEARYL ALCOHOL; .ALPHA.-TOCOPHEROL ACETATE; TROLAMINE; TRIETHOXYCAPRYLYLSILANE; TRIETHOXYSILYLETHYL POLYDIMETHYLSILOXYETHYL HEXYL DIMETHICONE; PREZATIDE; TRIPEPTIDE-10 CITRULLINE; GRAPE SEED OIL; WATER; XANTHAN GUM; CALENDULA OFFICINALIS FLOWER; CAMELLIA OLEIFERA LEAF; CAPRYLYL GLYCOL; CAPRYLYL TRISILOXANE; CELLULOSE ACETATE; CETYL ALCOHOL; CHAMOMILE; CHLORPHENESIN; CITRAL; CITRIC ACID MONOHYDRATE; CUCUMBER; CYCLOMETHICONE; CYCLOMETHICONE 5; DIMETHICONE; EDETATE DISODIUM ANHYDROUS; ETHYLHEXYL PALMITATE; ACAI; GLYCERIN; GLYCERYL MONOSTEARATE; .ALPHA.-HEXYLCINNAMALDEHYDE; HYDROXYETHYL ACRYLATE/SODIUM ACRYLOYLDIMETHYL TAURATE COPOLYMER (100000 MPA.S AT 1.5%); FERRIC OXIDE RED; FERRIC OXIDE YELLOW; FERROSOFERRIC OXIDE; LAURYL PEG-9 POLYDIMETHYLSILOXYETHYL DIMETHICONE; LIMONENE, (+)-; LINALOOL, (+/-)-; MAGNESIUM STEARATE; METHYL IONONES; NIACINAMIDE; PANTHENOL; PEG-100 STEARATE; PENTYLENE GLYCOL; POLYSORBATE 60; PROPANEDIOL; PROPYLENE GLYCOL MONOSTEARATE; PROPYLENE GLYCOL; PYRIDOXINE HYDROCHLORIDE; SODIUM CITRATE; HYALURONATE SODIUM; SODIUM PYRROLIDONE CARBOXYLATE; THERMUS THERMOPHILUS LYSATE; TRIETHOXYCAPRYLYLSILANE; WATER; STEARYL ALCOHOL; .ALPHA.-TOCOPHEROL ACETATE; TROLAMINE; PREZATIDE; TRIPEPTIDE-10 CITRULLINE; GRAPE SEED OIL; XANTHAN GUM; 1,2-HEXANEDIOL; ALLANTOIN; ALOE VERA LEAF; ALUMINUM OXIDE; BENZYL BENZOATE; BENZYL SALICYLATE; BIOTIN; BORON NITRIDE; BUTYLENE GLYCOL; ALKYL (C12-15) BENZOATE

HydroPeptide S.P.F. Sun Protection Friends

Active Ingredients

Titanium Dioxide 1.25%, Zinc Oxide 2.5%.

Purpose

Sunscreen

Uses

• Helps prevent sunburn.

Warnings

Spending time in the sun increases your risk of skin cancer and early skin aging. This product has been shown only to help prevent sunburn, not skin cancer or early skin aging. Skin Cancer/Skin Aging Alert:

Do not use

on damaged or broken skin.

When using this product

keep out of eyes. Rinse with water to remove.

Stop use and ask a doctor

if rash occurs.

Keep out of reach of children.

If product is swallowed, get medical help or contact a Poison Control Center right away.

Directions

• Apply liberally and evenly 15 minutes before sun exposure. • Reapply at least every 2 hours. • Use a water-resistant sunscreen if swimming or sweating. • Children under 6 months of age: Ask a doctor

Inactive Ingredients

Alumina, Butylene Glycol, Butyrospermum Parkii (Shea) Butter, C12-15 Alkyl Benzoate, Caprylyl Glycol, Caprylyl Methicone, Carbomer, Ceteareth-20, Cetearyl Alcohol, Cetyl Alcohol, Chamomilla Recutita (Matricaria) Flower Extract, Chlorphenesin, Chondrus Crispus (Carrageenan), Cyclohexasiloxane, Cyclopentasiloxane, Glucose, Glycerin, Glyceryl Caprylate, Glyceryl Stearate, Glyceryl Undecylenate, Hydrolyzed Soy Protein, Hydrolyzed Wheat Protein, Isopropyl Myristate, Lauryl PEG-9 Polydimethylsiloxyethyl Dimethicone, Lecithin, Niacinamide, PEG-100 Stearate, Phenoxyethanol, Polyhydroxystearic Acid, Pseudoalteromonas Ferment Extract, Sodium PCA, Stearyl Alcohol, Tocopheryl Acetate, Triethanolamine, Triethoxycaprylylsilane, Triethoxysilylethyl Polydimethylsilozyethyl Hexyl Dimethicone, Tripeptide-1, Tripeptide-10 Citrulline, Vitis Vinifera (Grape) Seed Oil, Water (Aqua), Xanthan Gum

Active Ingredients

Titanium Dioxide 2.5%, Zinc Oxide 6%

PURPOSE

Sunscreen

Uses

• Helps prevent sunburn. • If used as directed with other sun protection measures (see), decreases the risk of skin cancer and early skin aging caused by the sun.
Directions

Warnings

Spending time in the sun increases your risk of skin cancer and early skin aging. This product has been shown only to help prevent sunburn, not skin cancer or early skin aging. Skin Cancer/Skin Aging Alert:

Do not use

on damaged or broken skin.

When using this product

keep out of eyes. Rinse with water to remove.

Stop use and ask a doctor

if rash occurs.

Keep out of reach of children.

If product is swallowed, get medical help or contact a Poison Control Center right away.

Directions

• Apply liberally and evenly 15 minutes before sun exposure. • Reapply at least every 2 hours. • Use a water-resistant sunscreen if swimming or sweating. • Spending time in the sun increases your risk of skin cancer and early skin aging. To decrease this risk, regularly use a sunscreen with a Broad Spectrum SPF value of 15 or higher and other sun protection measures including: • Limit time in the sun, especially from 10 a.m. - 2 p.m. • Wear long-sleeved shirts, pants, hats, and sunglasses. • Children under 6 months of age: Ask a doctor
Sun Protection Measures.

Inactive Ingredients

1,2-Hexanediol, Acrylates/Ammonium Methacrylate Copolymer, Allantoin, Aloe Barbadensis Leaf Juice, Alpinia Galanga Extract, Alumina, Benzyl Benzoate, Benzyl Salicylate, Biotin, Boron Nitride, Butylene Glycol, C12-15 Alkyl Benzoate, Calendula Officinalis Flower Extract, Camellia Oleifera Leaf Extract, Caprylyl Glycol, Caprylyl Methicone, Cellulose Acetate, Cetyl Alcohol, Chamomilla Recutita (Matricaria) Flower Extract, Chlorphenesin, Citral, Citric Acid, Cucumis Sativus (Cucumber) Fruit Extract, Cyclomethicone, Cyclopentasiloxane, Dimethicone, Disodium EDTA, Ethylhexyl Palmitate, Euterpe Oleracea Fruit Extract, Fragrance (Parfum), Glycerin, Glyceryl Stearate, Hexyl Cinnamal, Hydrolyzed Yeast Protein, Hydroxyethyl Acrylate/Sodium Acryloyldimethyl Taurate Copolymer, Iron Oxide (CI 77491), Iron Oxide (CI 77492), Iron Oxide (CI 77499), Lauryl Peg-9 Polydimethylsiloxyethyl Dimethiconez, Limonene, Linalool, Magnesium Stearate, Methyl Ionone, Niacinamide, Panthenol, PEG-100 Stearate, Pentylene Glycol, Polyhydroxystearic Acid, Polysorbate 60, Propanediol, Propylene Glycol Stearate, Propylene Glycol, Pyridoxine HCl, Sodium Citrate, Sodium Hyaluronate, Sodium PCA, Thermus Thermophilus Ferment, Triethoxycaprylylsilane, Triethoxysilylethyl Polydimethylsiloxyethyl Dimethicone, Water (Aqua), Xanthan Gum, Stearyl Alcohol, Tocopheryl Acetate, Triethanolamine, Triethoxycaprylylsilane, Triethoxysilylethyl Polydimethylsilozyethyl Hexyl Dimethicone, Tripeptide-1, Tripeptide-10 Citrulline, Vitis Vinifera (Grape) Seed Oil, Water (Aqua), Xanthan Gum

Other Information

Protect the products in this container from excessive heat and direct sun.

Questions or comments?

Call 1.800.932.9873